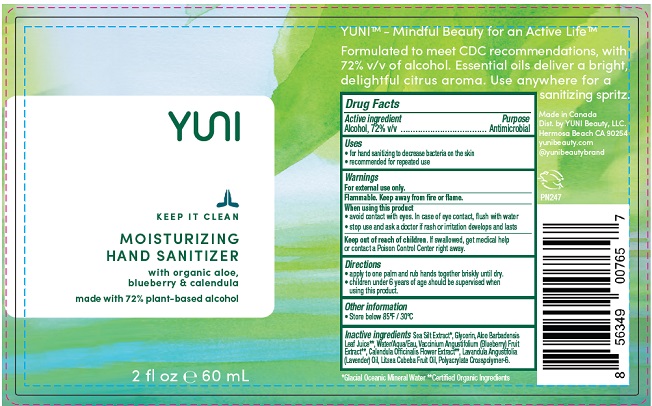 DRUG LABEL: Yuni beauty hand sanitizer
NDC: 76570-001 | Form: LIQUID
Manufacturer: YUNI Beauty LLC
Category: otc | Type: HUMAN OTC DRUG LABEL
Date: 20211021

ACTIVE INGREDIENTS: ALCOHOL 72 mL/100 mL
INACTIVE INGREDIENTS: GLYCERIN; ALOE VERA LEAF; WATER; LOWBUSH BLUEBERRY; CALENDULA OFFICINALIS FLOWER; LAVENDER OIL; LITSEA OIL; AMMONIUM ACRYLOYLDIMETHYLTAURATE, DIMETHYLACRYLAMIDE, LAURYL METHACRYLATE AND LAURETH-4 METHACRYLATE COPOLYMER, TRIMETHYLOLPROPANE TRIACRYLATE CROSSLINKED (45000 MPA.S)

Active Ingredient

Alcohol 72% v/v.

Purpose

Antimicrobial

Uses

- for hand sanitizing to decrease bacteria on the skin.
- recommended for repeated use.

Warnings

For external use only.

Flammable. Keep away from heat or flame.

When using this product

- avoid contact with eyes. In case of eye contact, flush with water.
- stop use and ask a doctor if rash or irritation develops and lasts.

Keep out of reach of children. If swallowed, get medical help or contact a Poison Control Center right away.

Directions

- apply to one palm and rub hands together briskly until dry.
- children under 6 years of age should be supervised when using this product.

Other information

- Store below 85ºF / 30ºC

Inactive ingredients

Sea Silt Extract*, Glycerin, Aloe Barbadensis Leaf Juice**, Water/Aqua/Eau, Vaccinium Angustifolium (Blueberry) Fruit Extract**, Calendula Officinalis Flower Extract**, Lavandula Angustifolia (Lavender) Oil, Litsea Cubeba Fruit Oil, Polyacrylate Crosspolymer-6.

*Glacial Oceanic Mineral Water **Certified Organic Ingredients